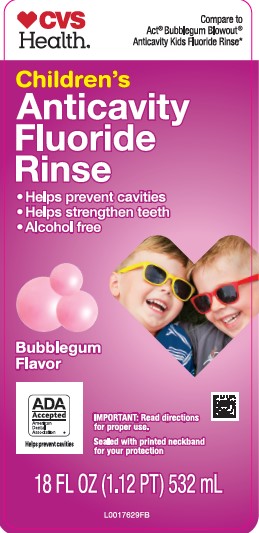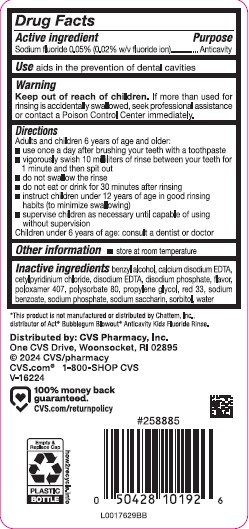 DRUG LABEL: Anticavity Fluoride Rinse
NDC: 59779-004 | Form: MOUTHWASH
Manufacturer: CVS Pharmacy, Inc.
Category: otc | Type: HUMAN OTC DRUG LABEL
Date: 20260202

ACTIVE INGREDIENTS: SODIUM FLUORIDE 0.2 mg/1 mL
INACTIVE INGREDIENTS: EDETATE CALCIUM DISODIUM ANHYDROUS; CETYLPYRIDINIUM CHLORIDE; EDETATE DISODIUM ANHYDROUS; SODIUM PHOSPHATE, DIBASIC, ANHYDROUS; POLOXAMER 407; POLYSORBATE 80; PROPYLENE GLYCOL; D&C RED NO. 33; SODIUM BENZOATE; SODIUM PHOSPHATE; SACCHARIN SODIUM; SORBITOL; BENZYL ALCOHOL; WATER

CVS 004.002/004AE
Anticavity Fluoride Rinse, Bubble Gum

Active ingredient

Sodium fluoride 0.05% (0.02%w/v fluoride ion)

Purpose

Anticavity

Use

aids in the prevention of dental cavities

Warning

for this product

Keep out of reach of children.

If more than used for rinsing is accidentally swallowed, seek professional assistance or contact a Poison Control Center immediately.

Directions

Adults and children 6 years of age and older:

- use once a day after brushing your teeth with a toothpaste
- vigorously swish 10 milliliters of rinse between your teeth for 1 minute and then spit out
- do not swallow the rinse
- do not eat or drink for 30 minutes after rinsing
- instruct children under 12 years of age in good rinsing habits (to minimize swallowing)
- supervise children as necessary until capable of using without supervision

Children under 6 years of age: consult a dentist or doctor

Other Information

- store at room temperature

Inactive ingredients

benzyl alcohol, calcium disodium EDTA, cetylpyridinium chloride, disodium EDTA, disodium phosphate, flavor, poloxamer 407, polysorbate 80, propylene glycol, red 33, sodium benzoate, sodium phosphate, sodium saccharin, sorbitol, water

Disclaimer

*This product is not manufactured or distributed by Chattem, Inc., distributor of Act Bubblegum Blowout Anticavity Kids Fluoride Rinse.

Adverse reaction

Distributed by CVS Pharmacy, Inc.

One CVS Drive, Woonsocket, RI 02895

© 2024 CVS/pharmacy

CVS.com® 1-800-shop-CVS

V-16224

100% money back guaranteed.

CVS.com/returnpolicy

Empty & Replace Cap

PLASTIC BOTTLE

how2recycle.info

principal display panel

CVS

Health

Compare to ACT® Bubble Gum Blowout® Anticavity Kids Fluoride Rinse*

Children's

ANTICAVITY FLUORIDE RINSE

- Helps prevent cavities
- Helps Strengthen Teeth
- Alcohol free

Bubblegum Flavor

ADA

Accepted

American

Dental

Association®

Helps prevent cavities

IMPORTANT: Read directions for proper use.

Sealed with printed neckband for your protection

18 FL OZ (1.12 PT) 532mL